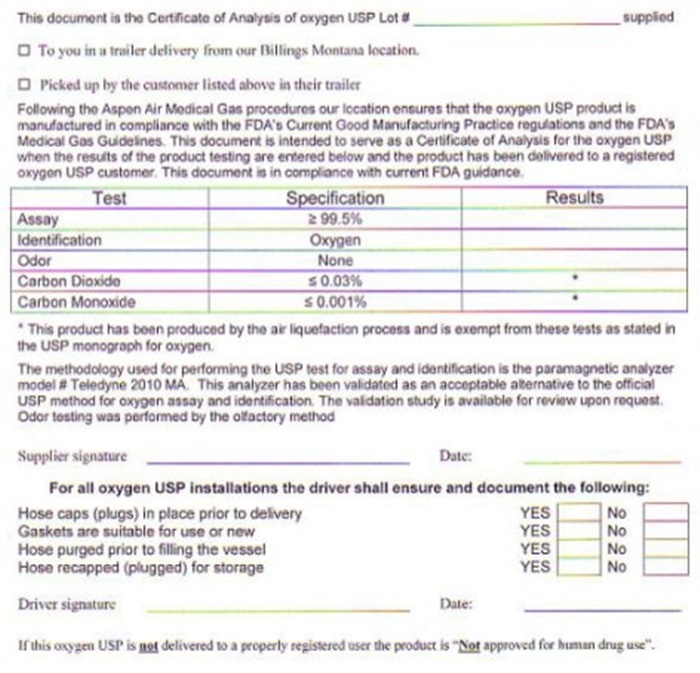 DRUG LABEL: OXYGEN
NDC: 42914-001 | Form: GAS
Manufacturer: Aspen Air U.S., LLC
Category: prescription | Type: HUMAN PRESCRIPTION DRUG LABEL
Date: 20241010

ACTIVE INGREDIENTS: OXYGEN 99 L/100 L

OXYGEN - 001

OXYGEN CERTIFICATE OF ANALYSIS

THIS DOCUMENT IS THE CERTIFICATE OF ANALYSIS OF OXYGEN USP LOT # ______________________ SUPPLIED TO YOU IN A TRAILER FROM OUR BILLINGS MONTANA LOCATION OR PICKED UP BY THE CUSTOMER LISTED ABOVE IN THEIR TRAILER. FOLLOWING THE ASPEN AIR MEDICAL GAS PROCEDURES OUR LOCATION ENSURES THAT THE OXYGEN USP PRODUCT IS MANUFACTURED IN COMPLIANCE WITH THE FDA'S CURRENT GOOD MANUFACTURING PRACTICE REGULATIONS AND THE FDA'S MEDICAL GAS GUIDELINES. THIS DOCUMENT IS INTENDED TO SERVE AS A CERTIFICATE OF ANALYSIS FOR THE OXYGEN USP WHEN THE RESULTS OF THE PRODUCT TESTING ARE ENTERED BELOW AND THE PRODUCT HAS BEEN DELIVERED TO A REGISTERED OXYGEN USP CUSTOMER. THIS DOCUMENT IS IN COMPLIANCE WITH CURRENT FDA GUIDANCE

TEST SPECIFICATIONS RESULTS

ASSAY GREATER THAN 99.5%

IDENTIFICATION OXYGEN

ODOR NONE

CARBON DIOXIDE LESS THAN 0.03%

CARBON MONOXIDE LESS THAN 0.001%

THE METHODOLOGY USED FOR PERFORMING THE USP TEST FOR ASSAY AND IDENTIFICATION IS THE PARAMAGNETIC ANALYZER MODEL # TELEDYNE 2010 MA. THIS ANALYZER HAS BEEN VALIDATED AS AN ACCEPTABLE ALTERNATIVE TO THE OFFICIAL USP METHOD FOR OXYGEN ASSAY AND IDENTIFICATION. THE VALIDATION STUDY IS AVAILABLE FOR REVIEW UPON REQUEST. ODOR TESTING WAS PERFORMED BY THE OLFACTORY METHOD. SUPPLIER SIGNATURE _________________________ DATE _________________

NUMBER 33 110 A1 - REVISION DATE 05/01/08

FOR ALL OXYGEN USP INSTALLATIONS THE DRIVER SHALL ENSURE AND DOCUMENT THE FOLLOWING: HOSECAPS (PLUGS) IN PLACE PRIOR TO DELIVERY YES/NO, GASKETS ARE SUITABLE FOR USE OR NEW YES/NO, HOSE PURGED PRIOR TO FILLING THE VESSEL YES/NO, HOSE RECAPED (PLUGGED) FOR STORAGE YES/NO. DRIVER SIGNATURE:____________________ DATE:_________________